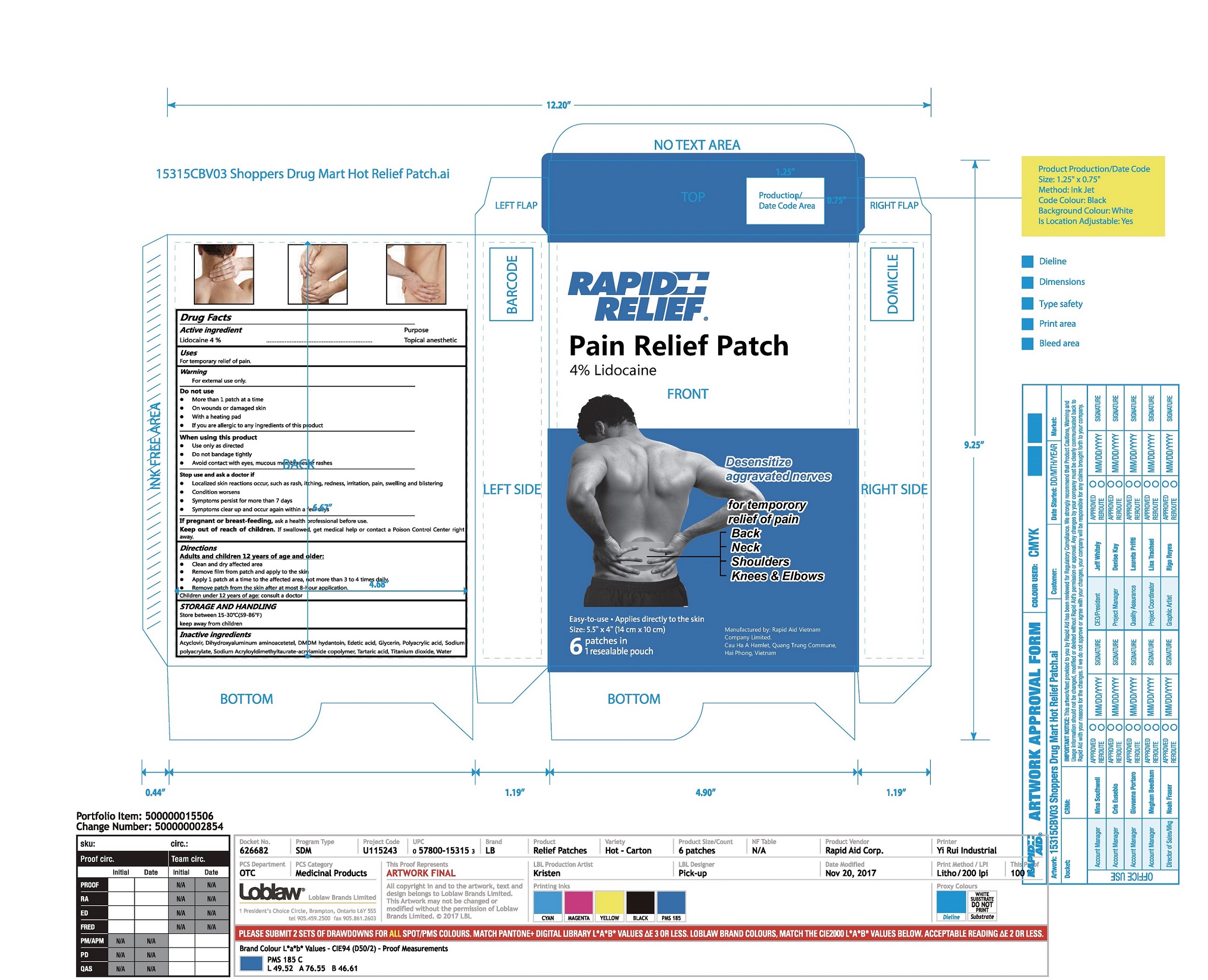 DRUG LABEL: Rapid Relief Pain Relief Patch
NDC: 83569-002 | Form: PATCH
Manufacturer: RAPID AID VIET NAM CO., LTD
Category: otc | Type: HUMAN OTC DRUG LABEL
Date: 20251016

ACTIVE INGREDIENTS: LIDOCAINE 4 g/100 g
INACTIVE INGREDIENTS: ACYCLOVIR; POLYACRYLIC ACID (450000 MW); DIHYDROXYALUMINUM AMINOACETATE; GLYCERIN; WATER; DMDM HYDANTOIN; EDETIC ACID; SODIUM POLYACRYLATE (8000 MW); SODIUM ACRYLOYLDIMETHYLTAURATE-ACRYLAMIDE COPOLYMER (1:1; 90000-150000 MPA.S); TARTARIC ACID; TITANIUM DIOXIDE

Active Ingredient(s)

Lidocaine 4 % w/w.

Purpose

Topical analgesic

Use

Temporary relief of minor pain.

Warnings

For external use only.

Do not use

 More than 1 patch at a time
 On wounds or damaged skin
 With a heating pad
 If you are allergic to any ingredients of this product

When using this product:

 Use only as directed
 Do not bandage tightly
 Avoid contact with eyes, mucous membranes or rashes

Stop use and ask a doctor if:

 Localized skin reactions occur, such as rash, itching, redness, irritation, pain, swelling and blistering
 Condition worsens
 Symptoms persist for more than 7 days
 Symptoms clear up and occur again within a few days

If pregnant or breastfeeding, ask a health professional before use.

KEEP OUT OF REACH OF CHILDREN

If swallowed, get medical help or contact a Poison Control Center right away.

Directions

Adults and children 12 years of age and older:
 Clean and dry affected area
 Remove film from patch and apply to the skin
 Apply 1 patch at a time to the affected area, not more than 3 to 4 times daily.
 Remove patch from the skin after at most 8-hour application.
Children under 12 years of age: consult a doctor

STORAGE AND HANDLING

Store between 15-30℃(59-86℉) keep away from children

Inactive ingredients

Acyclovir, Dihydroxyaluminum aminoacetetel, DMDM hydantoin, Edetic acid, Glycerin, Polyacrylic acid, Sodium polyacrylate, Sodium Acryloyldimethyltaurate-acrylamide copolymer, Tartaric acid, Titanium dioxide, Wate